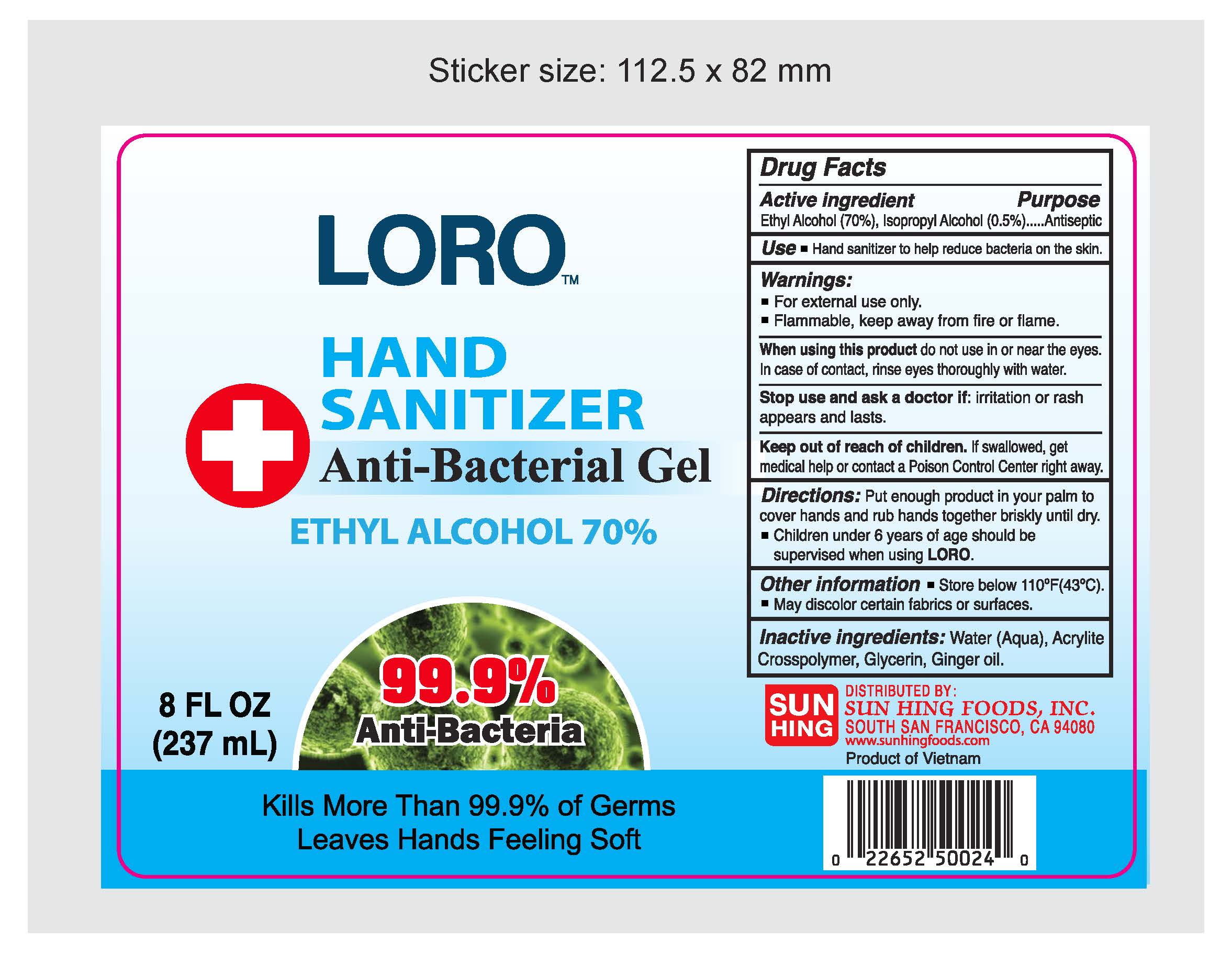 DRUG LABEL: LORO Hand Sanitizer
NDC: 78185-010 | Form: GEL
Manufacturer: Sun Hing Foods Inc
Category: otc | Type: HUMAN OTC DRUG LABEL
Date: 20200330

ACTIVE INGREDIENTS: ALCOHOL 70 mL/237 mL; ISOPROPYL ALCOHOL 0.2 mL/237 mL
INACTIVE INGREDIENTS: GINGER OIL 0.05 mL/237 mL; GLYCERIN 0.25 mL/237 mL; WATER 29 mL/237 mL; CARBOMER INTERPOLYMER TYPE A (55000 CPS) 0.5 mL/237 mL

LORO
HAND SANITIZER
Anti-Bacterial Gel
ETHYL ALCOHOL 70%
8 FL OZ (237 mL)

This is a hand sanitizer manufactured according to the Temporary Policy for Preparation of Certain Alcohol-Based Hand Sanitizer Products During the Public Health Emergency (CoViD-19); Guidance for Industry.

The hand sanitizer is manufactured using only the following United States Pharmacopoeia (USP) grade ingredients in the preparation of the product (percentage in final product formulation) consistent with World Health Organization (WHO) recommendations:

1. Alcohol (ethanol) (USP or Food Chemical Codex (FCC) grade) (70%, volume/volume (v/v)) in an aqueous solution denatured according to Alcohol and Tobacco Tax and Trade Bureau regulations in 27 CFR part 20.
2. Glycerol (0.25% v/v).
3. Isopropyl Alcohol (0.2% v/v).
4. Sterile distilled water or boiled cold water (29% v/v).
5. Acrylite Crosspolymer (0.5% v/v).
6. Ginger Oil (0.05% v/v)

The firm does not add other active or inactive ingredients. Different or additional ingredients may impact the quality and potency of the product.

Active Ingredient(s)

Tehyl Alcohol 70% v/v, Isopropyl Alcohol 0.5%. Purpose: Antiseptic

Purpose

Antiseptic, Hand Sanitizer

Use

Hand Sanitizer to help reduce bacteria on the skin.

Warnings

For external use only. Flammable. Keep away from heat or flame

Do not use

- Children under 6 years of age should be supervised when using LORO

When using this product keep out of eyes, ears, and mouth. In case of contact with eyes, rinse eyes thoroughly with water.
Stop use and ask a doctor if irritation or rash occurs. These may be signs of a serious condition.
Keep out of reach of children. If swallowed, get medical help or contact a Poison Control Center right away.

Stop use and ask a doctor if irritation or rash appears and lasts.

Keep out of reach of children. If swallowed, get medical help or contact a Poison Control Center right away.

Directions

- Place enough product on hands to cover all surfaces. Rub hands together until dry.
- Supervise children under 6 years of age when using this product to avoid swallowing.

Other information

- Store below 110 Degree F (43 Degree C)
- May discolor certain fabrics or surfaces

Manufacture By:

Hanoi Biology Chemistry Group Corporation

252/57 Tay Son, Trung Liet Ward, Dong Da District,

Hanoi, Vietnam

Inactive ingredients

Water (Aqua), Acrylite Crosspolymer, Glycerine, Ginger Oil.

Package Label - Principal Display Panel

237 mL NDC: 78185-010-01